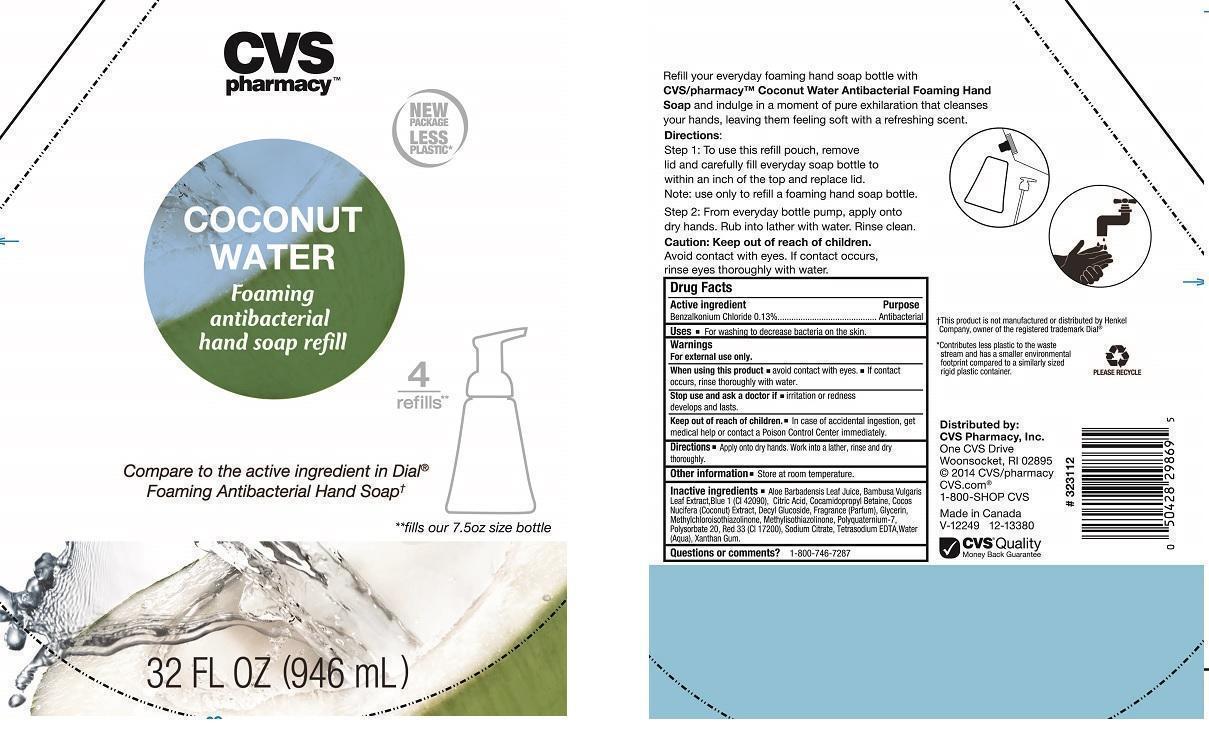 DRUG LABEL: CVS PHARMACY
NDC: 59779-842 | Form: LIQUID
Manufacturer: CVS PHARMACY
Category: otc | Type: HUMAN OTC DRUG LABEL
Date: 20140127

ACTIVE INGREDIENTS: BENZALKONIUM CHLORIDE 1.3 mg/1 mL
INACTIVE INGREDIENTS: ALOE VERA LEAF; BAMBUSA VULGARIS LEAF; FD&C BLUE NO. 1; CITRIC ACID ACETATE; COCAMIDOPROPYL BETAINE; COCONUT OIL; DECYL GLUCOSIDE; GLYCERIN; METHYLCHLOROISOTHIAZOLINONE; METHYLISOTHIAZOLINONE; POLYQUATERNIUM-7 (70/30 ACRYLAMIDE/DADMAC; 1600000 MW); POLYSORBATE 20; D&C RED NO. 33; SODIUM CITRATE; EDETATE SODIUM; WATER; XANTHAN GUM

DRUG FACTS

ACTIVE INGREDIENT

BENZALKONIUM CHLORIDE 0.13%

PURPOSE

ANTIBACTERIAL

USES

FOR WASHING TO DECREASE BACTERIA ON THE SKIN

WARNINGS

FOR EXTERNAL USE ONLY

WHEN USING THIS PRODUCT

AVOID CONTACT WITH EYES. IF CONTACT OCCURS, RINSE THOROUGHLY WITH WATER

STOP USE AND ASK A DOCTOR IF

IRRITATION OR REDNESS DEVELOPS AND LASTS

KEEP OUT OF REACH OF CHILDREN

IN CASE OF ACCIDENTAL INGESTION, GET MEDICAL HELP OR CONTACT A POISON CONTROL CENTER IMMEDIATELY

DIRECTIONS

APPLY ONTO DRY HANDS. WORK INTO A LATHER, RINSE AND DRY THOROUGHLY

OTHER INFORMATION

STORE AT ROOM TEMPERATURE

INACTIVE INGREDIENTS

ALOE BARBADENSIS LEAF JUICE, BAMBUSA VULGARIS LEAF EXTRACT, BLUE 1 (CI 42090), CITRIC ACID, COCAMIDOPROPYL BETAINE, COCOS NUCIFERA (COCONUT) EXTRACT, DECYL GLUCOSIDE, FRAGRANCE (PARFUM), GLYCERIN, METHYLCHLOROISOTHIAZOLINONE, METHYLISOTHIAZOLINONE, POLYQUATERNIUM-7, POLYSORBATE 20, RED 33 (CI 17200), SODIUM CITRATE, TETRASODIUM EDTA, WATER (AQUA), XANTHAN GUM

QUESTIONS OR COMMENTS?

1-800-746-7287